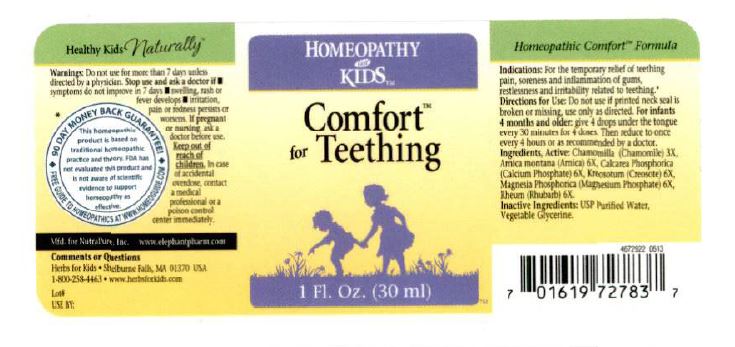 DRUG LABEL: Comfort for Teething
NDC: 64616-115 | Form: LIQUID
Manufacturer: Vitality Works, Inc.
Category: homeopathic | Type: HUMAN OTC DRUG LABEL
Date: 20251217

ACTIVE INGREDIENTS: MAGNESIUM PHOSPHATE, MONOBASIC, UNSPECIFIED 6 [hp_X]/0.05 mL; CHAMOMILE 3 [hp_X]/0.05 mL; ARNICA MONTANA 6 [hp_X]/0.05 mL; TRIBASIC CALCIUM PHOSPHATE 6 [hp_X]/0.05 mL; WOOD CREOSOTE 6 [hp_X]/0.05 mL; RHEUM OFFICINALE ROOT 6 [hp_X]/0.05 mL
INACTIVE INGREDIENTS: WATER; GLYCERIN

Comfort for Teething

Directions for Use:

Do not use if printed neck seal is broken or missing use only as directed. For infants 4 months and older: give 4 drops under the tongue every 30 minutes for 4 doses. Then reduce to once every 4 hours or as recommended by a doctor.

Ingredients, Active:

Chamomilla (Chamomile) 3X, Arnica montana (Arnica) 6X, Calcarea phosphorica (Calcium phosphate)6x, Kreosotum (Creosote) 6X, Magensia phosphorica (Magnesium phosphate) 6X, Rheum (Rhubarb) 6X.

Inactive ingredients

USP Purified water, Vegetable glycerine

Warnings:

Do not use for more than 7 days unless directed by a physician. Stop use and ask a doctor if

- symptoms do not improve in 7 days
- swelling, rash, or fever develops
- irritiation, pain or redness persists or worsens

If pregnant or nursing, ask a doctor before use

Indications:

For the temporary relief of teething pain, soreness and inflammation of gums, restlessness and irritability related to teething.

Comments or Questions

Health for Kids Shelbourne Falls, MA 01370 USA

1-800-255-4463

www.herbsforkids.com

Keep out of reach of children. In case of accidental overdose, contact a medical professional or contact a poison control center immediately

INDICATIONS AND USAGE

For the temporary relief of teething pain, soreness and inflammation of gums, restlessness and irritability related to teething

comfort for teething label.jpg